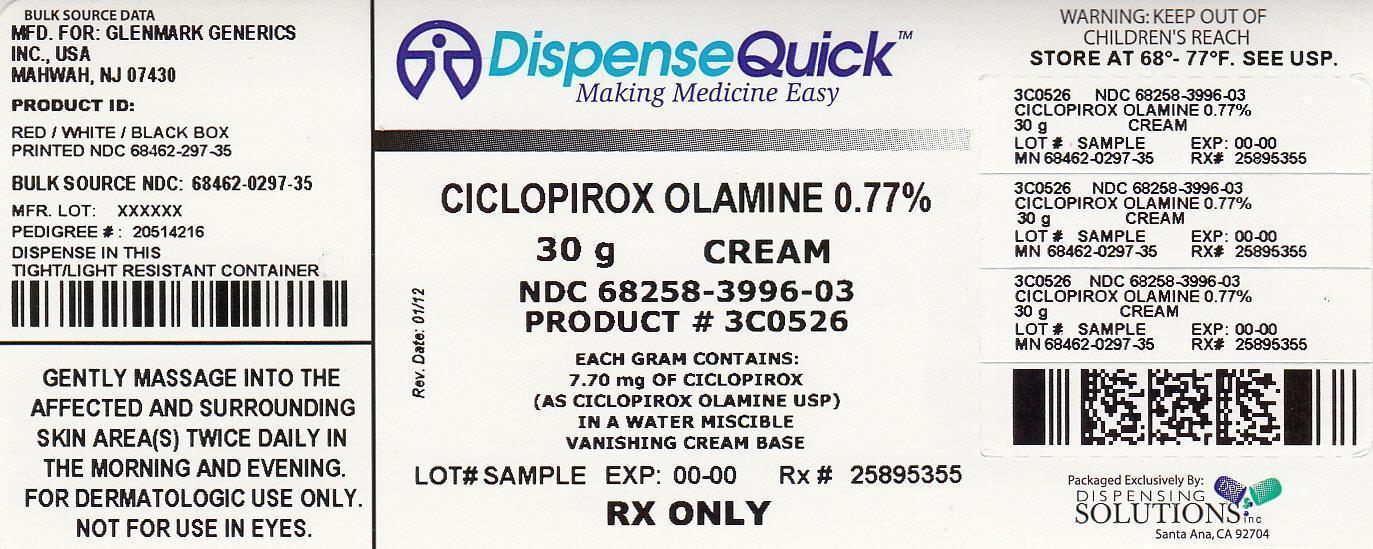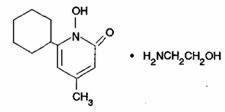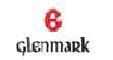 DRUG LABEL: Ciclopirox Olamine
NDC: 68258-3996 | Form: CREAM
Manufacturer: Dispensing Solutions, Inc.
Category: prescription | Type: HUMAN PRESCRIPTION DRUG LABEL
Date: 20121003

ACTIVE INGREDIENTS: CICLOPIROX OLAMINE 7.7 mg/1 g
INACTIVE INGREDIENTS: CETYL ALCOHOL; LIGHT MINERAL OIL; OCTYLDODECANOL; STEARYL ALCOHOL; POLYSORBATE 60; MYRISTYL ALCOHOL; SORBITAN MONOSTEARATE; LACTIC ACID; BENZYL ALCOHOL; WATER

Ciclopirox Olamine Cream USP, 0.77%

FOR DERMATOLOGIC USE ONLY.
NOT FOR USE IN EYES.

DESCRIPTION

Ciclopirox olamine cream USP, 0.77% is for topical use. Each gram of ciclopirox olamine cream USP contains 7.70 mg of ciclopirox (as ciclopirox olamine USP) in a water miscible vanishing cream base consisting of purified water USP, cetyl alcohol NF, light mineral oil NF, octyldodecanol NF, stearyl alcohol NF, polysorbate 60 NF, myristyl alcohol NF, sorbitan monostearate NF, lactic acid USP, and benzyl alcohol NF (1%) as preservative.

Ciclopirox olamine cream USP contains a synthetic, broad-spectrum, antifungal agent ciclopirox (as ciclopirox olamine USP). The chemical name is 6-cyclohexyl-1-hydroxy-4-methyl-2(1H)-pyridone, 2 -aminoethanol salt.

The CAS Registry Number is 41621-49-2. The chemical structure is:

CLINICAL PHARMACOLOGY

Ciclopirox is a broad-spectrum, antifungal agent that inhibits the growth of pathogenic dermatophytes, yeasts, and Malassezia furfur. Ciclopirox exhibits fungicidal activity in vitro against isolates of Trichophyton rubrum, Trichophyton mentagrophytes, Epidermophyton floccosum, Microsporum canis, and Candida albicans.

Pharmacokinetic studies in men with tagged ciclopirox solution in polyethylene glycol 400 showed an average of 1.3% absorption of the dose when it was applied topically to 750 cm^2 on the back followed by occlusion for 6 hours. The biological half-life was 1.7 hours and excretion occurred via the kidney. Two days after application only 0.01% of the dose applied could be found in the urine. Fecal excretion was negligible.

Penetration studies in human cadaverous skin from the back, with ciclopirox olamine cream with tagged ciclopirox showed the presence of 0.8 to 1.6% of the dose in the stratum corneum 1.5 to 6 hours after application. The levels in the dermis were still 10 to 15 times above the minimum inhibitory concentration.

Autoradiographic studies with human cadaverous skin showed that ciclopirox penetrated into the hair and through the epidermis and hair follicles into the sebaceous glands and dermis, while a portion of the drug remains in the stratum corneum.

Draize Human Sensitization Assay, 21-Day Cumulative Irritancy study, Phototoxicity study, and Photo-Draize study conducted in a total of 142 healthy male subjects showed no contact sensitization of the delayed hypersensitivity type, no irritation, no phototoxicity, and no photo-contact sensitization due to ciclopirox olamine cream.

INDICATIONS AND USAGE

Ciclopirox olamine cream is indicated for the topical treatment of the following dermal infections: tinea pedis, tinea cruris, and tinea corporis due to Trichophyton rubrum, Trichophyton mentagrophytes, Epidermophyton floccosum, and Microsporum canis; candidiasis (moniliasis) due to Candida albicans; and tinea (pityriasis) vesicolor due to Malassezia furfur.

CONTRAINDICATIONS

Ciclopirox olamine cream is contraindicated in individuals who have shown hypersensitivity to any of its components.

WARNINGS

Ciclopirox olamine cream is not for ophthalmic use.
Keep out of the reach of children.

PRECAUTIONS

If a reaction suggesting sensitivity or chemical irritation should occur with the use of ciclopirox olamine cream, treatment should be discontinued and appropriate therapy instituted.

Information for Patients

The patient should be told to:

1. Use the medication for the full treatment time even though symptoms may have improved and notify the physician if there is no improvement after four weeks.
2. Inform the physician if the area of application shows signs of increased irritation (redness, itching, burning, blistering, swelling, or oozing) indicative of possible sensitization.
3. Avoid the use of occlusive wrappings or dressings.

Carcinogenesis, Mutagenesis, Impairment of Fertility

A carcinogenicity study in female mice dosed cutaneously twice per week for 50 weeks followed by a 6-month drug-free observation period prior to necropsy revealed no evidence of tumors at the application site.

The following in vitro and in vivo genotoxicity tests have been conducted with ciclopirox olamine: studies to evaluate gene mutation in the Ames Salmonella/Mammalian Microsome Assay (negative) and Yeast Saccharomyces Cerevisiae Assay (negative) and studies to evaluate chromosome aberrations in vivo in the Mouse Dominant Lethal Assay and in the Mouse Micronucleus Assay at 500 mg/kg (negative).

The following battery of in vitro genotoxicity tests were conducted with ciclopirox: a chromosome aberration assay in V79 Chinese Hamster Cells, with and without metabolic activation (positive); a gene mutation assay in the HGPRT – test with V79 Chinese Hamster Cells (negative); and a primary DNA damage assay (i.e., unscheduled DNA Synthesis Assay in A549 Human Cells (negative). An in vitro Cell Transformation Assay in BALB/C3T3 Cells was negative for cell transformation. In an in vivo Chinese Hamster Bone Marrow Cytogenetic Assay, ciclopirox was negative for chromosome aberrations at 5,000 mg/kg.

Pregnancy Category B

Reproduction studies have been performed in the mouse, rat, rabbit, and monkey (via various routes of administration) at doses 10 times or more the topical human dose and have revealed no significant evidence of impaired fertility or harm to the fetus due to ciclopirox. There are, however, no adequate or well-controlled studies in pregnant woman. Because animal reproduction studies are not always predictive of human response, this drug should be used during pregnancy only if clearly needed.

Nursing Mothers

It is not known whether this drug is excreted in human milk. Because many drugs are excreted in human milk, caution should be exercised when ciclopirox olamine cream is administered to a nursing woman.

Pediatric Use

Safety and effectiveness in pediatric patients below the age of 10 years have not been established.

ADVERSE REACTIONS

In all controlled clinical studies with 514 patients using ciclopirox olamine cream and in 296 patients using the vehicle cream, the incidence of adverse reactions was low. This included pruritus at the site of application in one patient and worsening of the clinical signs and symptoms in another patient using ciclopirox olamine cream and burning in one patient and worsening of the clinical signs and symptoms in another patient using the vehicle cream.

DOSAGE AND ADMINISTRATION

Gently massage ciclopirox olamine cream into the affected and surrounding skin areas twice daily, in the morning and evening. Clinical improvement with relief of pruritus and other symptoms usually occurs within the first week of treatment. If a patient shows no clinical improvement after four weeks of treatment with ciclopirox olamine cream, the diagnosis should be redetermined. Patients with tinea versicolor usually exhibit clinical and mycological clearing after two weeks of treatment.

HOW SUPPLIED

Ciclopirox olamine cream USP, 0.77% is supplied in 15 gram (NDC 68462-297-17), 30 gram (NDC 68462-297-35) and 90 gram (NDC 68462-297-92) tubes.

STORAGE AND HANDLING

Store at 20-25oC (68-77oF) [see USP Controlled Room Temperature].

Manufactured by:

Glenmark Generics Ltd.
Colvale-Bardez, Goa 403 513, India

Manufactured for:

Glenmark Generics Inc., USA
Mahwah, NJ 07430

Questions? 1 (888)721-7115
www.glenmarkgenerics.com

February 2011

PRINCIPAL DISPLAY PANEL

NDC 68258-3996-03